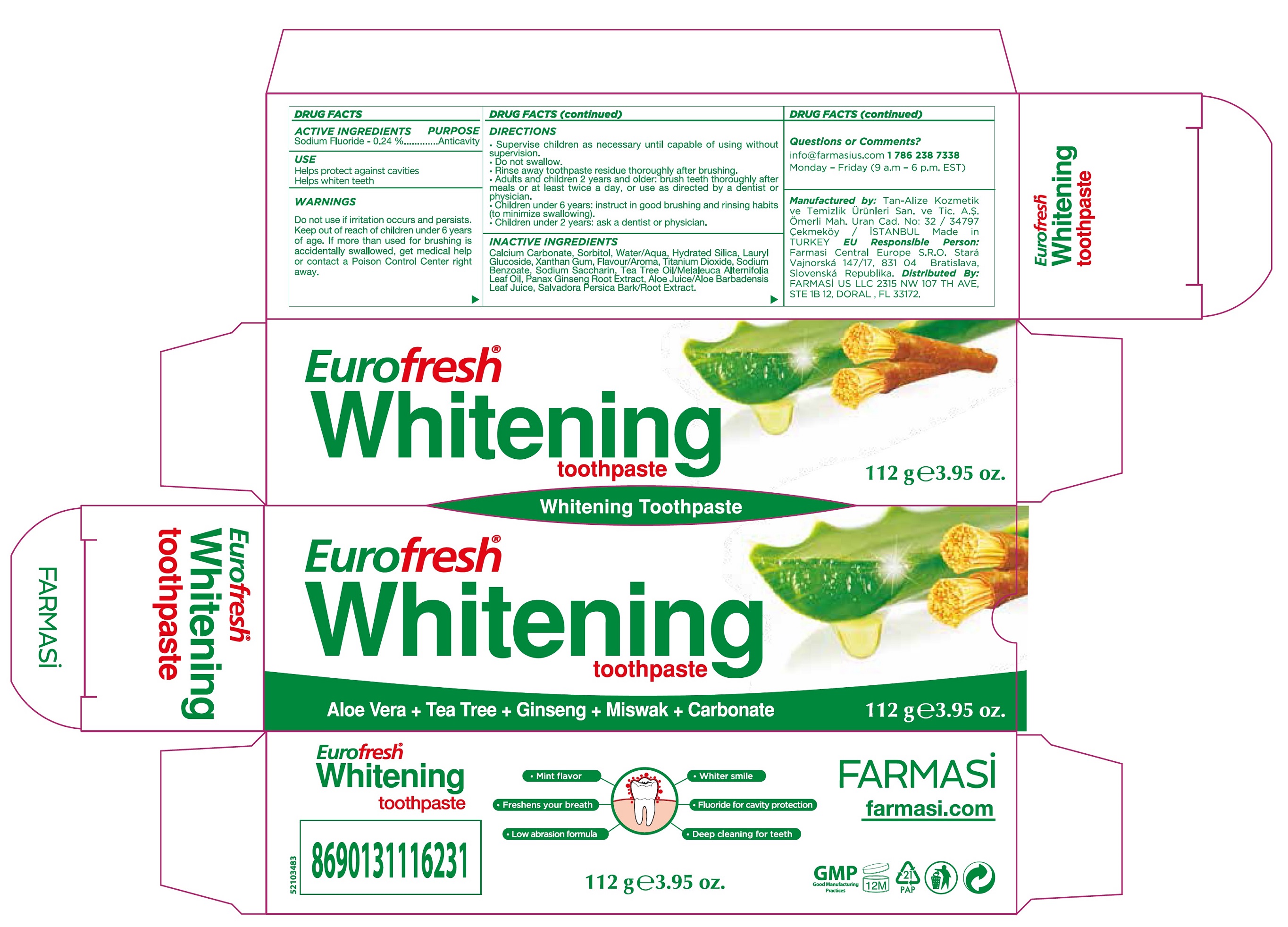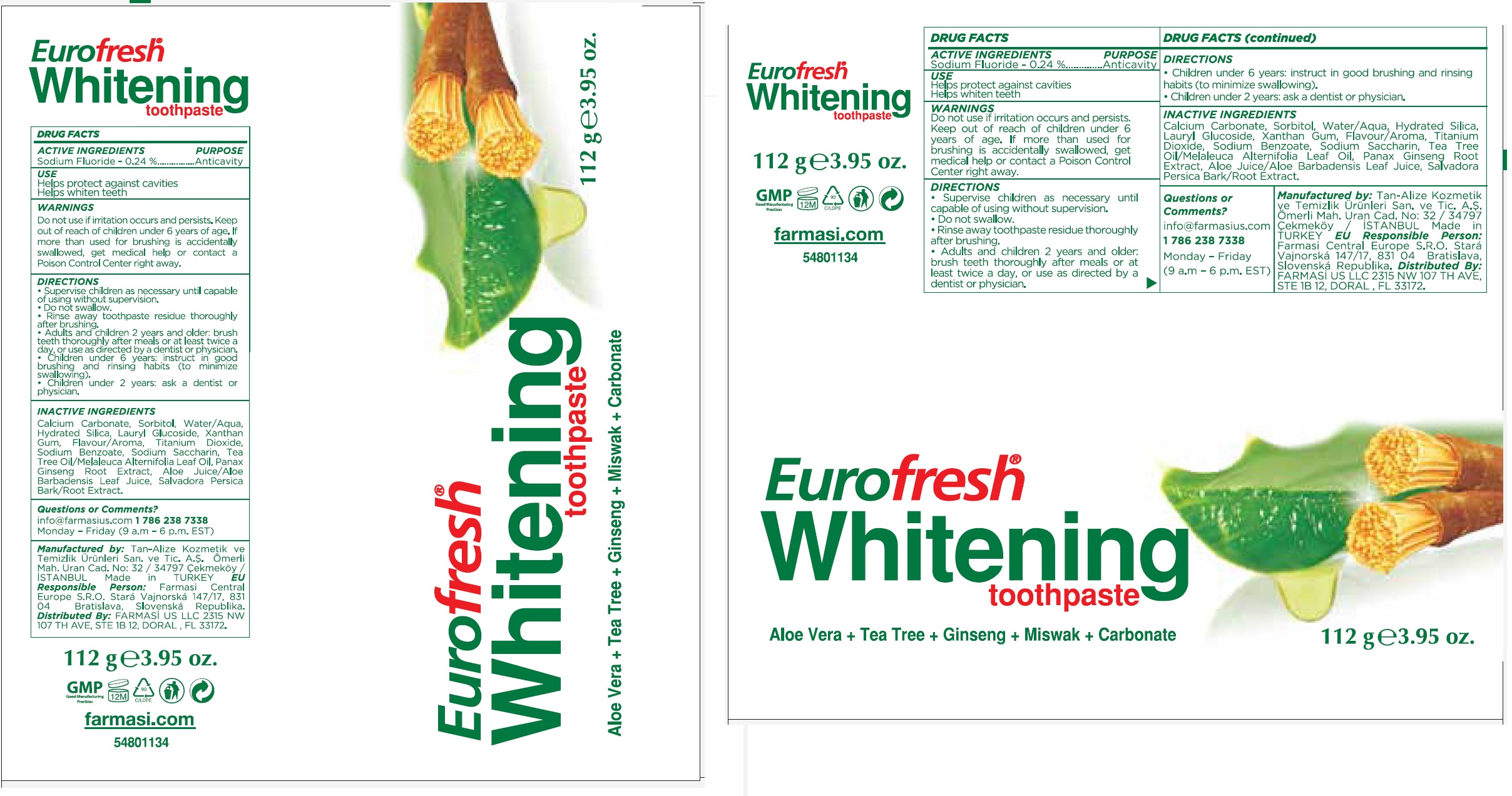 DRUG LABEL: Eurofresh Whitening
NDC: 74690-008 | Form: PASTE, DENTIFRICE
Manufacturer: Farmasi US LLC
Category: otc | Type: HUMAN OTC DRUG LABEL
Date: 20231105

ACTIVE INGREDIENTS: SODIUM FLUORIDE 1.08 mg/1 g
INACTIVE INGREDIENTS: CALCIUM CARBONATE; SORBITOL; WATER; HYDRATED SILICA; LAURYL GLUCOSIDE; XANTHAN GUM; TITANIUM DIOXIDE; SODIUM BENZOATE; SACCHARIN SODIUM; TEA TREE OIL; ASIAN GINSENG; ALOE VERA LEAF; SALVADORA PERSICA ROOT

Eurofresh Whitening Toothpaste

ACTIVE INGREDIENTS

Sodium Fluoride - 0.24%

PURPOSE

Anticavity

USE

Helps protect against cavities

Helps whiten teeth

WARNINGS

Do not use

if irritation occurs and persists.

Keep out of reach of children

under 6 years of age. If more than used for brushing is accidentally swallowed, get medical help or contact a Poison Control Center right away.

DIRECTION

- Supervise children as necessary until capable of using without supervision.
- Do not swallow.
- Rinse away toothpaste residue thoroughly after brushing.
- Adults and children 2 years and older: brush teeth thoroughly after meals or at least twice a day, or use as directed by a dentist or physician.
- Children under 6 years: instruct in good brushing and rinsing habits (to minimize swallowing).
- Children under 2 years: ask a dentist or physician.

INACTIVE INGREDIENTS

Calcium Carbonate, Sorbitol, Water/Aqua, Hydrated Silica, Lauryl Glucoside, Xanthan Gum, Flavour/Aroma, Titanium Dioxide, Sodium Benzoate, Sodium Saccharin, Tea Tree Oil/Melaleuca alternifolia Leaf Oil, Panax Ginseng Root Extract, aloe Juice Barbadensis Leaf juice, Salvadora Persica Bark/Root Extract.

Questions or Comments?

info@farmasius.com 1786 236 7338

Monday - Friday (9 a.m-6 p.m. EST)